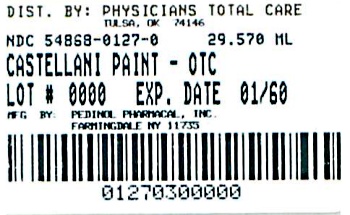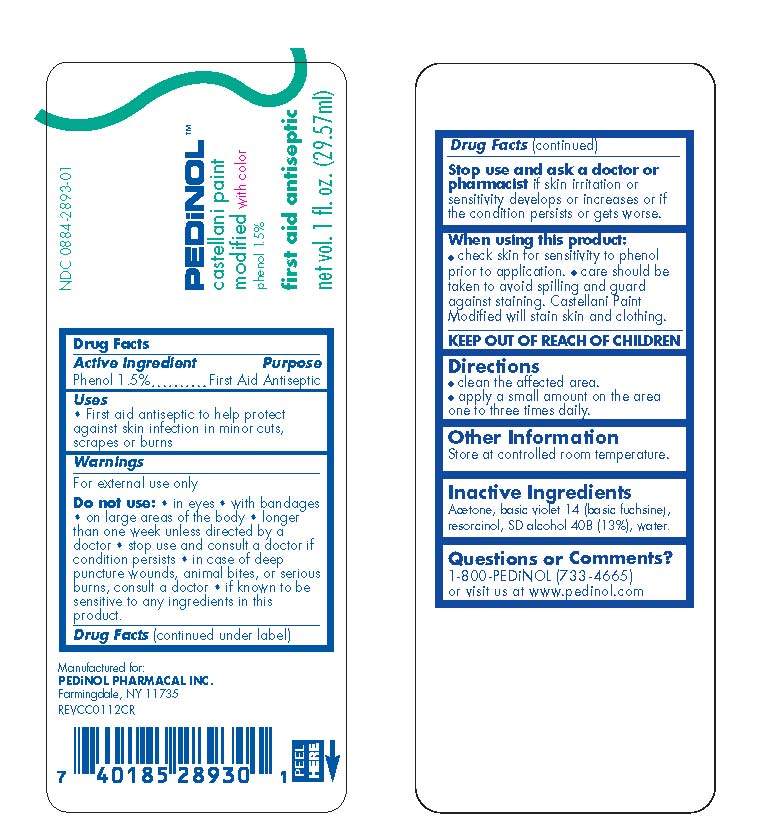 DRUG LABEL: Castellani Paint
NDC: 54868-0127 | Form: LIQUID
Manufacturer: Physicians Total Care, Inc.
Category: otc | Type: HUMAN OTC DRUG LABEL
Date: 20140515

ACTIVE INGREDIENTS: Phenol 15 mg/1 mL
INACTIVE INGREDIENTS: ACETONE; ROSANILINE HYDROCHLORIDE; RESORCINOL; ALCOHOL; Water

Castellani Paint Modified (with color)

Drug Facts

Active Ingredient

Phenol 1.5%

Purpose

First Aid Antiseptic

Uses

- First aid antiseptic to help protect against skin infection in minor cuts, scrapes or burns

Warnings

For external use only

Do not use

- in eyes
- with bandages
- on large areas of the body
- longer than one week unless directed by a doctor
- stop use and consult a doctor if condition persists
- in case of deep puncture wounds, animal bites, or serious burns, consult a doctor
- if known to be sensitive to any ingredients in this product,

Stop use and ask a doctor or pharmacist if skin irritation or sensitivity develops or increases or if the condition persists or gets worse.

When using this product

- check skin for sensitivity to phenol prior to application.
- care should be taken to avoid spilling and guard against staining. Castellani Paint Modified will stain skin and clothing.

KEEP OUT OF REACH OF CHILDREN.

Directions

- clean the affected area
- apply a small amount on the area one to three times daily.

Other Information

Store at controlled room temperature.

Inactive Ingredients

Acetone, basic violet 14 (basic fuchsine), resorcinol, SD alcohol 40B (13%), water.

Questions or Comments?

1-800-PEDiNOL (733-4665) or visit us at www.pedinol.com

PRINCIPAL DISPLAY PANEL - 29.57 mL Bottle Label

PEDiNOL™

castellani paint

modified with color

phenol 1.5%

first aid antiseptic

net vol. 1 fl. oz. (29.57 ml)

Distributed by:

Physicians Total Care, Inc.

Tulsa, OK 74146

NDC 54868-0127-0